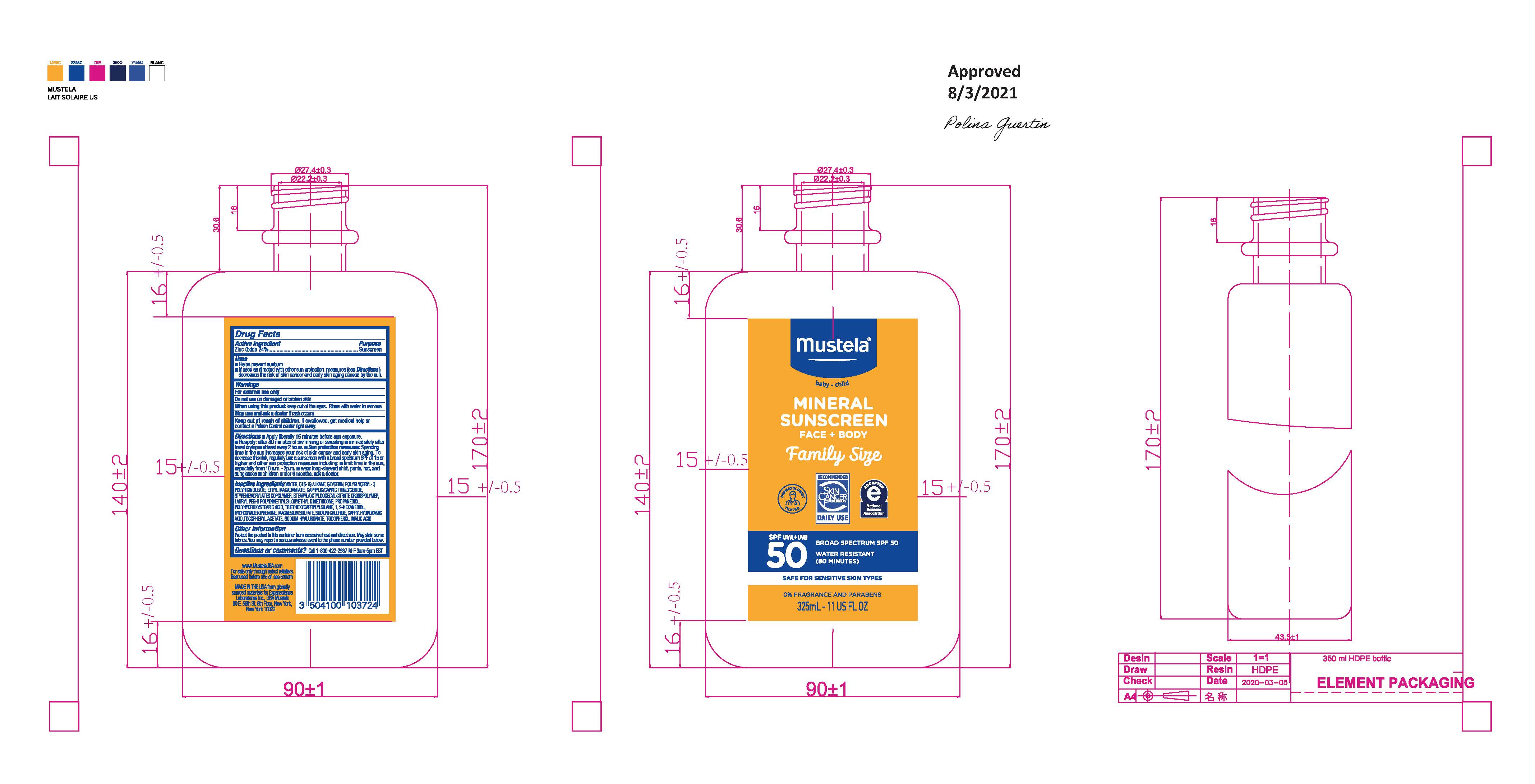 DRUG LABEL: Cream
NDC: 61354-089 | Form: CREAM
Manufacturer: Oxygen Development LLC
Category: otc | Type: HUMAN OTC DRUG LABEL
Date: 20230202

ACTIVE INGREDIENTS: ZINC OXIDE 24.05 mg/100 mg
INACTIVE INGREDIENTS: 1,2-HEXANEDIOL 0.9 mg/100 mg; HYDROXYACETOPHENONE 0.5 mg/100 mg; MAGNESIUM SULFATE, UNSPECIFIED 0.5 mg/100 mg; WATER 31.495 mg/100 mg; STYRENE 2.91 mg/100 mg; PROPANEDIOL 1.95 mg/100 mg; SODIUM CHLORIDE 0.5 mg/100 mg; STEARYL/OCTYLDODECYL CITRATE CROSSPOLYMER 2 mg/100 mg; MEDIUM-CHAIN TRIGLYCERIDES 3 mg/100 mg; LAURYL PEG-9 POLYDIMETHYLSILOXYETHYL DIMETHICONE 1.99 mg/100 mg; POLYHYDROXYSTEARIC ACID (2300 MW) 1 mg/100 mg; TRIETHOXYCAPRYLYLSILANE 0.95 mg/100 mg; ETHYL MACADAMIATE 3.99 mg/100 mg; C15-19 ALKANE 15 mg/100 mg; POLYGLYCERYL-3 PENTARICINOLEATE 4 mg/100 mg; GLYCERIN 4.98 mg/100 mg

MUSTELA MINERAL SUNSCREEN FACE+BODY FAMILY SIZE

Active ingredient

Zinc Oxide 24%

Purpose

Sunscreen

Uses

Help prevent sunburn. If used as directed with other sun protection measures (see Directions), decreases the risk of cancer and early skin caused by the sun.

Warnings

For external use only. Do not use on damaged or broken skin.

When using

When using this product keep out of the eyes. rinse with water to remove.

Keep out of reach of children. If swallowed, get medical help or contact a Poison Control center right away

Directions

Apply liberally 15 minutes before sun exposure. Reapply: after 80 minutes of swimming or sweating. Immediately after towel drying. At least every 2 hours. Sun protection measures: Spending time in the sun increases your risk of skin cancer and early skin aging. To decrease the risk, regularly use a sunscreen with a broad spectrum SPF of 15 or higher and other sun protection measures including: limit time in the sun, especially from 10 am - 2 pm. Wear long-sleeved shirt, pants, hat, and sunglasses. Children under 6 months: ask a doctor

Inactive ingredient

Water/Aqua, C15-19 Alkane, Glycerin, Polyglyceryl-3 Polyricinoleate, Ethyl Macadamiate, Caprylic/Capric Triglyceride, Styrene/Acrylates Copolymer, Stearyl/Octyldodecyl Citrate Crosspolymer, Lauryl PEG-9 Polydimethylsiloxyethyl Dimethicone, Propanediol, Polyhydroxystearic Acid, Triethoxycaprylylsilane, 1,2-Hexanediol, Hydroxyacetophenone, Magnesium Sulfate, Sodium Chloride, Caprylhydroxamic Acid, Tocopheryl Acetate, Sodium Hyaluronate, Tocopherol, Malic Acid

Other information

Protect the product in this container from excessive heat and direct sun. May stain some fabrics. You may report a serious adverse event to the phone number provided below.